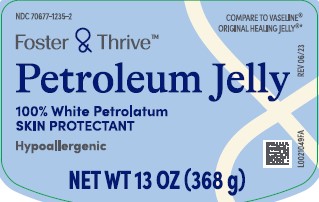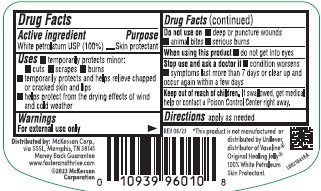 DRUG LABEL: Petroleum
NDC: 70677-1235 | Form: JELLY
Manufacturer: Strategic Sourcing Services LLC
Category: otc | Type: HUMAN OTC DRUG LABEL
Date: 20260217

ACTIVE INGREDIENTS: PETROLATUM 1 g/1 g

Foster & Thrive 069.001/069AA
Petroleum Jelly

Active ingredient

White Petrolatum USP (100%)

Purpose

Skin Protectant

Use

- temporarily protects minor:
- cuts
- scrapes
- burns
- temporarily protects and helps relieve chapped or cracked skin and lips
- helps protect from the drying effects of wind and cold weather

Warnings

For external use only

Do not use on

- deep or punture wounds
- animal bites
- serious burns

When using this product

- do not get into eyes

Stop use and ask a doctor if

- condition worsens
- symptoms last more than 7 days or clear up and occur again within a few days

Keep out of reach of children.

If swallowed, get medical help or contact a Poison Control Center right away.

Directions

Apply as needed

Inactive ingredients

None

Adverse Reaction

Distributed by: Mckesson Corp., via SSSL

Memphis, TN 38141

Money Back Guarantee

www.fosterandthrive.com

©2023 McKesson Corporation

*This product is not manufactured or distributed by Unilever, distributor of Vaseline® Original Healing Jelly®100% White Petroleum Skin Protectant.

Principal display panel

NDC 70677-1235-2

COMPARE TO VASELINE® ORIGINAL HEALING JELLY®*

Foster & Thrive™

Petroleum Jelly

100% White Petrolatum

SKIN PROTECTANT

Hypoallergenic

NET WT 13 OZ (368 g)